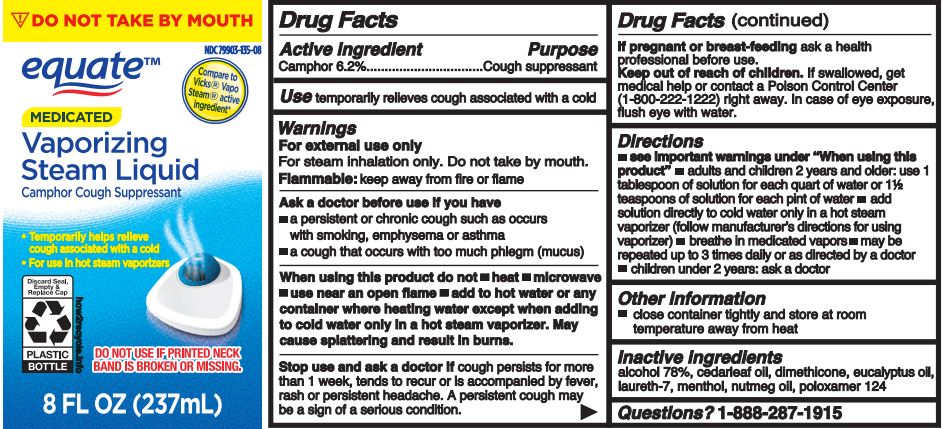 DRUG LABEL: Equate
NDC: 79903-135 | Form: LIQUID
Manufacturer: Walmart Inc.
Category: otc | Type: HUMAN OTC DRUG LABEL
Date: 20251008

ACTIVE INGREDIENTS: CAMPHOR (SYNTHETIC) 6.23 g/10 mL
INACTIVE INGREDIENTS: DIMETHICONE; POLOXAMER 124; CEDAR LEAF OIL; EUCALYPTUS GLOBULUS LEAF; LAURETH-7; ALCOHOL; MENTHOL; NUTMEG OIL

Equate Vaporizing Steam Liquid

Active ingredient

Camphor 6.2%

Purpose

Cough Suppressant

Use

temporarily relieves cough associated with a cold

Warnings

For external use only

For steam inhalation only. Do not take by mouth.

Flammable: keep away from fire or flame

Ask a doctor before use if you have

- a persistent or chronic cough such as occurs with smoking, emphysema or asthma
- a cough that occurs with too much phlegm (mucus)

When using this product do not

- heat
- microwave
- use near an open flame
- take by mouth
- add to hot water or any container where heating water except when adding to cold water only in a hot steam vaporizer. May cause splattering and result in burns.

Stop use and ask a doctor if

cough persists for more than 1 week, tends to recur or is accompanied by fever, rash or persistent headache. A persistent cough may be a sign of a serious condition.

If pregnant or breast-feeding

ask a health professional before use.

Keep out of reach of children.

If swallowed, get medical help or contact a Poison Control Center (1-800-222-1222) right away. In case of eye exposure, flush eye with water.

Directions

- see important warnings under "When using this product"
- adults & children 2 years & over:
- use 1 tablespoon of solution for each quart of water or 1½ teaspoonful of solution for each pint of water
- add solution directly to cold water only in a hot steam vaporizer (follow manufacturer's directions for using vaporizer)
- breathe in the medicated vapors
- use up to three times daily or as directed by a doctor
- children under 2 years: ask a doctor

Other information

close container tightly and store at room temperature away from heat

Inactive ingredient

alcohol (78%), cedarleaf oil, dimethicone, eucalyptus oil, laureth-7, menthol, nutmeg oil, poloxamer 124